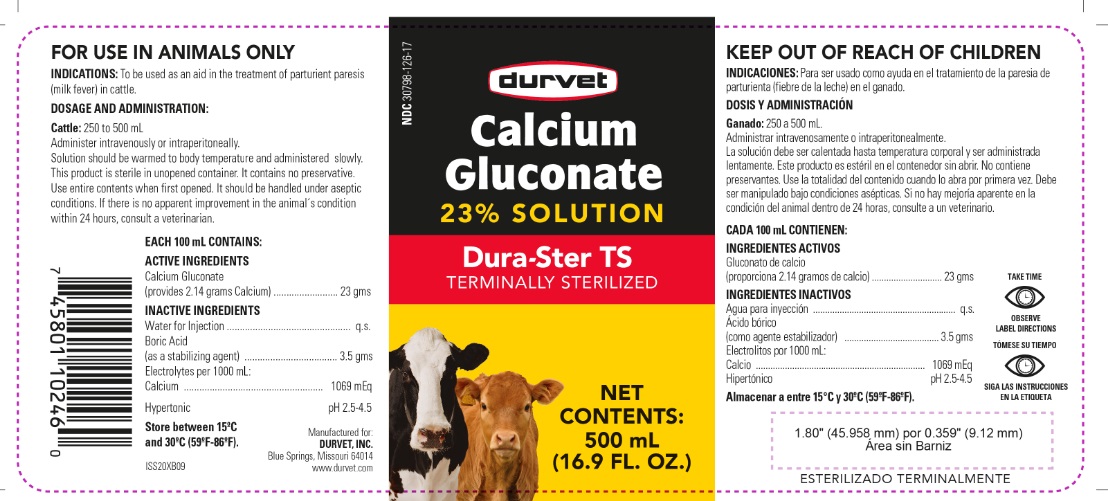 DRUG LABEL: Calcium Gluconate
NDC: 30798-126 | Form: INJECTION, SOLUTION
Manufacturer: Durvet
Category: animal | Type: OTC ANIMAL DRUG LABEL
Date: 20210713

ACTIVE INGREDIENTS: CALCIUM GLUCONATE 23 g/100 mL

CALCIUM GLUCONATE 23% SOLUTION

GENERAL PRECAUTIONS

FOR USE IN ANIMALS ONLY

EACH 100 mL CONTAINS: ACTIVE INGREDIENTS

Calcium Gluconate
(provides 2.14 grams Calcium) ...................23 grams

INACTIVE INGREDIENTS

Water for Injection ................................,,,,,,.....q.s.

Boric acid
(as a solubilizing agent) ......................... .3.5 grams

Electrolytes per 1000 mL: Calcium.............1069 mEq

Hypertonic pH 2.5-4.5

INDICATIONS:

To be used as an aid in the treatment of parturient paresis (milk fever) in cattle.

STORAGE AND HANDLING

Store between 15°C and 30°C (59°F-86°F)

KEEP OUT OF REACH OF CHILDREN

DOSAGE AND ADMINISTRATION:

Cattle: 250 to 500 mL

Administer intravenously or intraperitoneally. Solution should be warmed to body temperature and administered slowly. This product is sterile in unopened container. It contains no preservative. Use entire contents when first opened. It should be handled under aseptic conditions. If there is no apparent improvement in the animal's condition within 24hours, consult a veterinarian.

GENERAL PRECAUTIONS

TAKE TIME OBSERVE LABEL DIRECTIONS

INFORMATION FOR OWNERS/CAREGIVERS

ISS20XB09

Manufactured for:
DURVET, INC.
Blue Springs, MO 64014
www.durvet.com

PACKAGE LABEL

NDC 30798-126-17

durvet

Calcium Gluconate 23% SOLUTION

Dura-Ster TS

TERMINALLY STERILIZED

NET CONTENTS: 500 mL (16.9 fl. oz.)